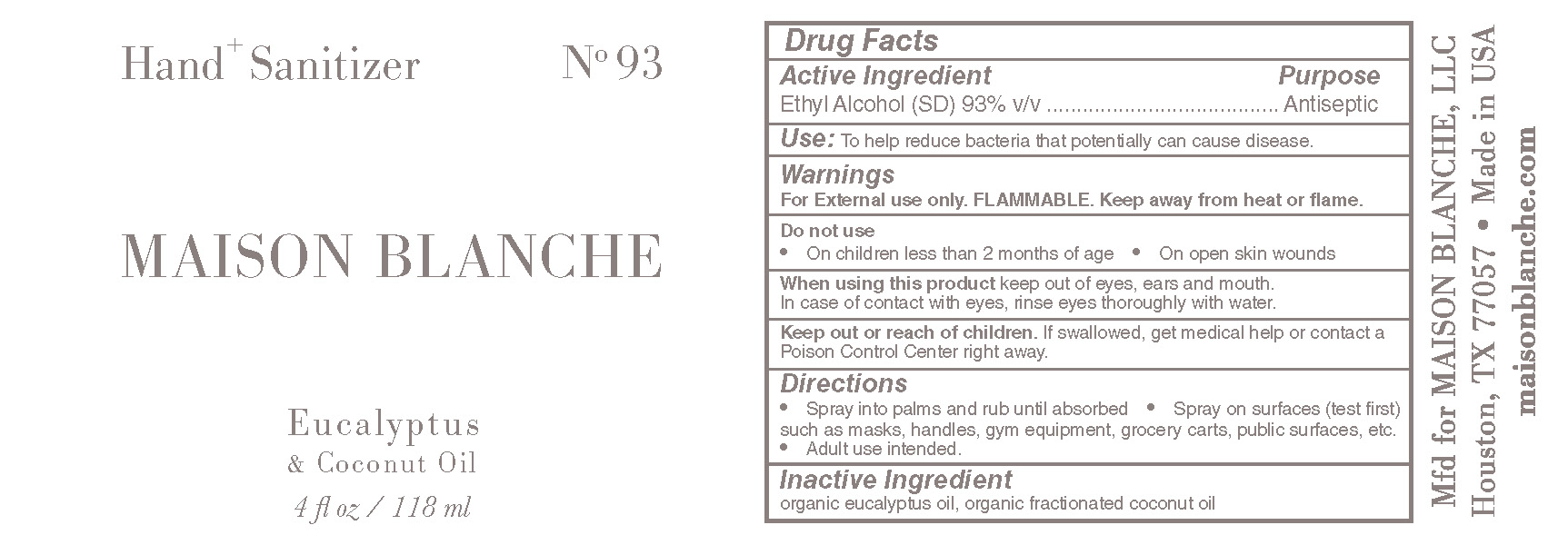 DRUG LABEL: Maison Blanche
NDC: 78966-111 | Form: LIQUID
Manufacturer: Maison Blanche LLC
Category: otc | Type: HUMAN OTC DRUG LABEL
Date: 20221017

ACTIVE INGREDIENTS: ALCOHOL 93 mL/100 mL
INACTIVE INGREDIENTS: MEDIUM-CHAIN TRIGLYCERIDES; EUCALYPTUS OIL

Maison Blanche Hand+ Sanitizer

Active Ingredient(s)

Alcohol 93% v/v. Purpose: Antiseptic

Purpose

Antiseptic, Hand Sanitizer

Use

To help reduce bacteria that potentially can cause disease.

Warnings

For external use only. Flammable. Keep away from heat or flame

Do not use

- in children less than 2 months of age
- on open skin wounds
- on skin burns

When using this product keep out of eyes, ears, and mouth. In case of contact with eyes, rinse eyes thoroughly with water.
Stop use and ask a doctor if irritation or rash occurs. These may be signs of a serious condition.
Keep out of reach of children. If swallowed, get medical help or contact a Poison Control Center right away.

Stop use and ask a doctor if irritation or rash occurs. These may be signs of a serious condition.

Keep out of reach of children. If swallowed, get medical help or contact a Poison Control Center right away.

Directions

Spray into palms and rub until absorbed.

Spray on the surfaces (test first) such as masks, handles, gym equipment, grocery cart, public surfaces, etc.

Adult use intended only.

Inactive ingredients

Eucalyptus oil,, coconut oil.

Package Label - Principal Display Panel

118 mL NDC: 78966-111-12